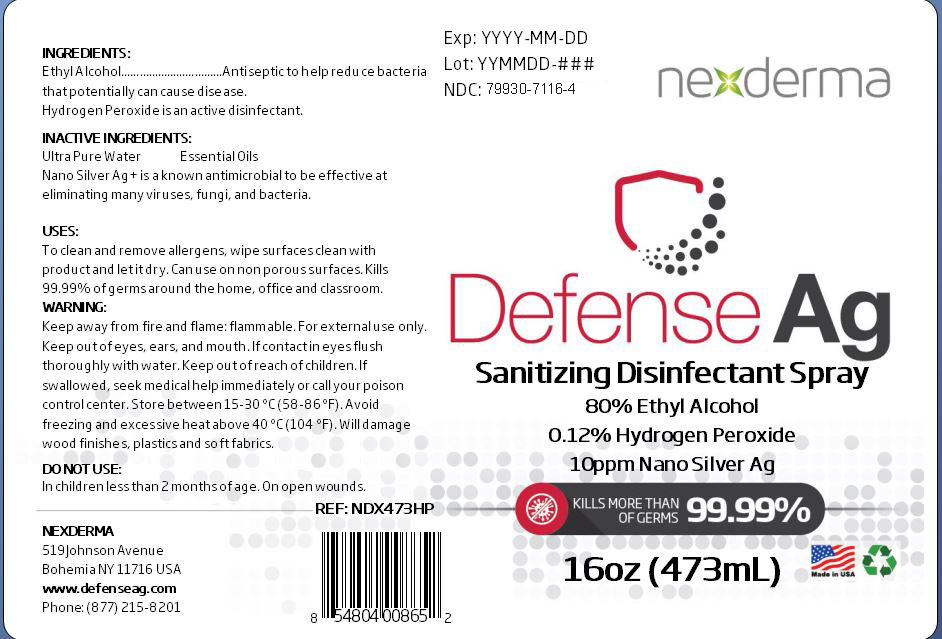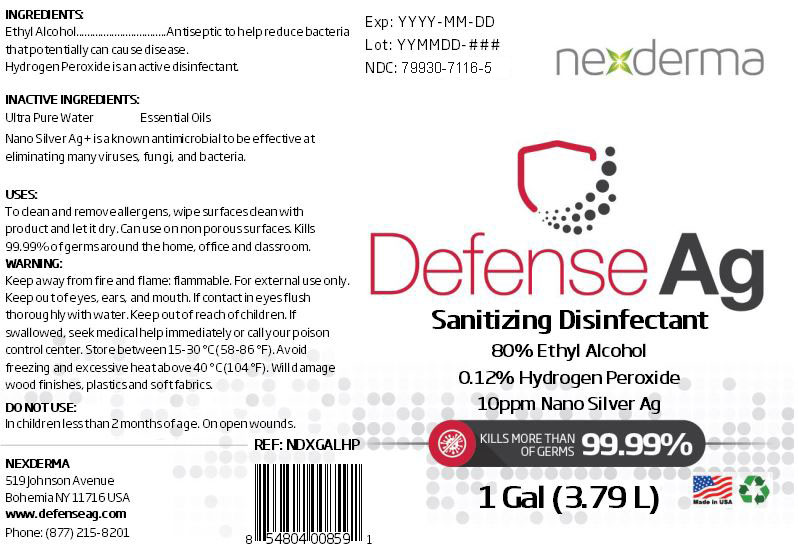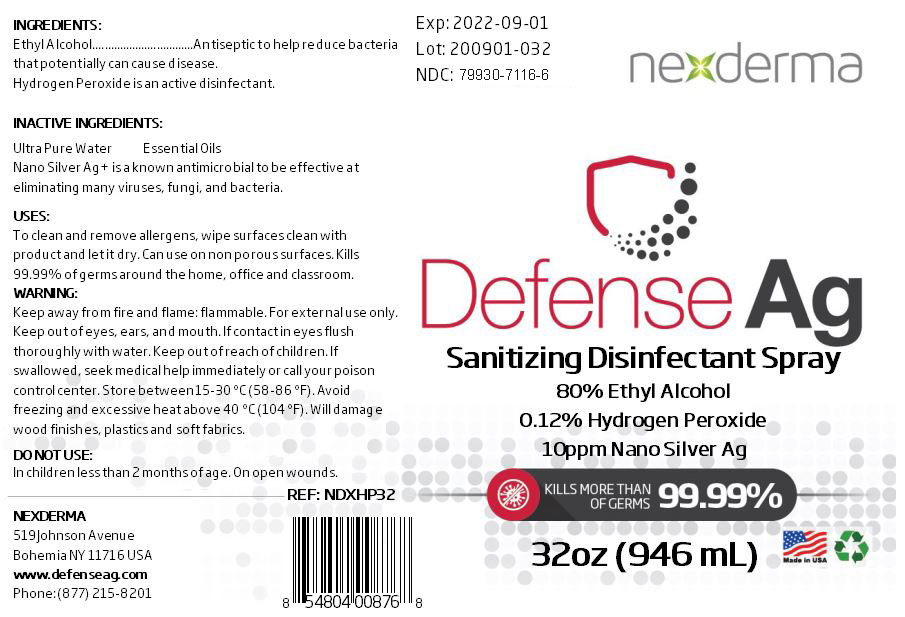 DRUG LABEL: Defense AG Disinfectant
NDC: 79930-7116 | Form: SPRAY
Manufacturer: Nexderma
Category: otc | Type: HUMAN OTC DRUG LABEL
Date: 20201104

ACTIVE INGREDIENTS: HYDROGEN PEROXIDE 0.125 mL/100 mL; ALCOHOL 80 mL/100 mL
INACTIVE INGREDIENTS: SILVER 0.2 mL/100 mL; WATER

EA Defense AG Disinfectant - New 2

Active Ingredient(s)

Alcohol 80% v/v. Purpose: Antiseptic to help reduce bacteria that potentially can cause disease.

Hydrogen Peroxide

Inactive ingredients

ultra pure water, Nano Silver Ag+

Use

To clean and remove allergens, wipe surfaces clean with product and let dry. Can use on porous surfaces. Kills 99.99% of germs around the home, office and classroom.

Keep out of reach of children. If swallowed, get medical help or contact a Poison Control Center right away.

Warnings

For external use only. Flammable. Keep away from heat or flame

Do not use

- in children less than 2 months of age
- on open skin wounds

Directions

- Spray enough product to cover all surfaces. Wipe clean and let it dry.
- Supervise children under 6 years of age when using this product to avoid swallowing.

Purpose

Antiseptic to help reduce bacteria that potentially can cause disease.

Package Label - Principal Display Panel

473 mL NDC: 79930-7116-4

946 mL NDC: 79930-7116-6

3790 mL NDC: 79930-7116-5